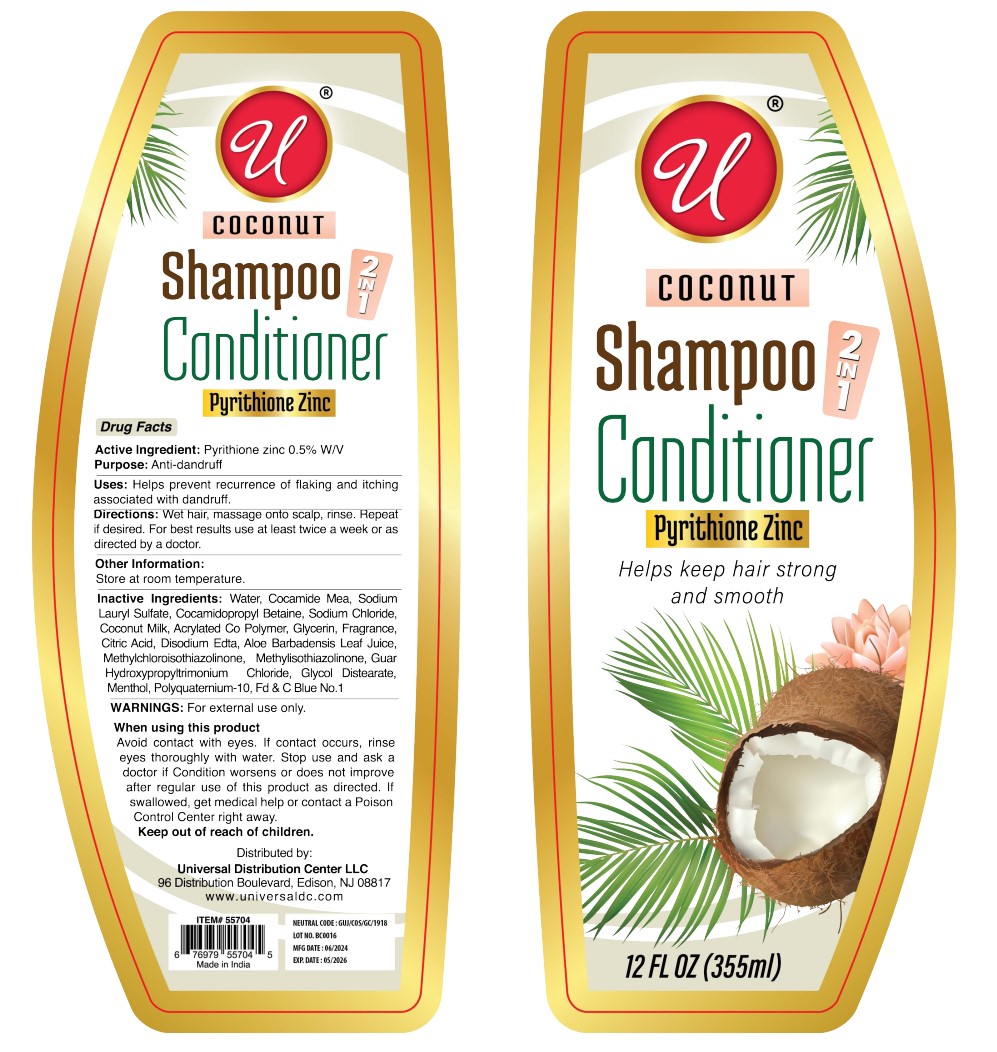 DRUG LABEL: Pyrithione Zinc 0.5 2in1 Dandruff Conditioner
NDC: 52000-415 | Form: SHAMPOO
Manufacturer: Universal Distribution Center LLC
Category: otc | Type: HUMAN OTC DRUG LABEL
Date: 20240517

ACTIVE INGREDIENTS: PYRITHIONE ZINC 0.5 g/100 mL
INACTIVE INGREDIENTS: WATER; COCO MONOETHANOLAMIDE; SODIUM LAURYL SULFATE; COCAMIDOPROPYL BETAINE; SODIUM CHLORIDE; COCONUT; BUTYL ACRYLATE/METHYL METHACRYLATE/METHACRYLIC ACID COPOLYMER (18000 MW); GLYCERIN; CITRIC ACID MONOHYDRATE; EDETATE DISODIUM; ALOE VERA LEAF; METHYLCHLOROISOTHIAZOLINONE; METHYLISOTHIAZOLINONE; GUAR HYDROXYPROPYLTRIMONIUM CHLORIDE; GLYCOL DISTEARATE; MENTHOL, UNSPECIFIED FORM; POLYQUATERNIUM-10 (400 MPA.S AT 2%); FD&C BLUE NO. 1

COCONUT Shampoo Conditioner 2IN1

Active Ingredient:

Pyrithione zinc 0.5% W/V

Purpose:

Anti-dandruff

Uses:

Helps prevent recurrence of flaking and itching associated with dandruff.

Directions:

Wet hair, massage onto scalp, rinse. Repeat if desired. For best results use at least twice a week or as directed by a doctor.

Other Information:

Store at room temperature.

Inactive Ingredients:

Water, Cocamide Mea, Sodium Lauryl Sulfate, Cocamidopropyl Betaine, Sodium Chloride, Coconut Milk, Acrylated Co Polymer, Glycerin, Fragrance, Citric Acid, Disodium Edta, Aloe Barbadensis Leaf Juice, Methylchloroisothiazolinone, Methylisothiazolinone, Guar Hydroxypropyltrimonium Chloride, Glycol Distearate, Menthol, Polyquaternium-10, Fd & C Blue No.1

WARNINGS:

For external use only.

When using this product
Avoid contact with eyes. If contact occurs, rinse eyes thoroughly with water. Stop use and ask a doctor if Condition worsens or does not improve after regular use of this product as directed. If swallowed, get medical help or contact a Poison Control Center right away.

Keep out of reach of children.

U COCONUT Shampoo Conditioner 2IN1

Helps keep hair strong and smooth

Distributed by:
Universal Distribution Center LLC
96 Distribution Boulevard, Edison, NJ 08817
www.universaldc.com

Made in India